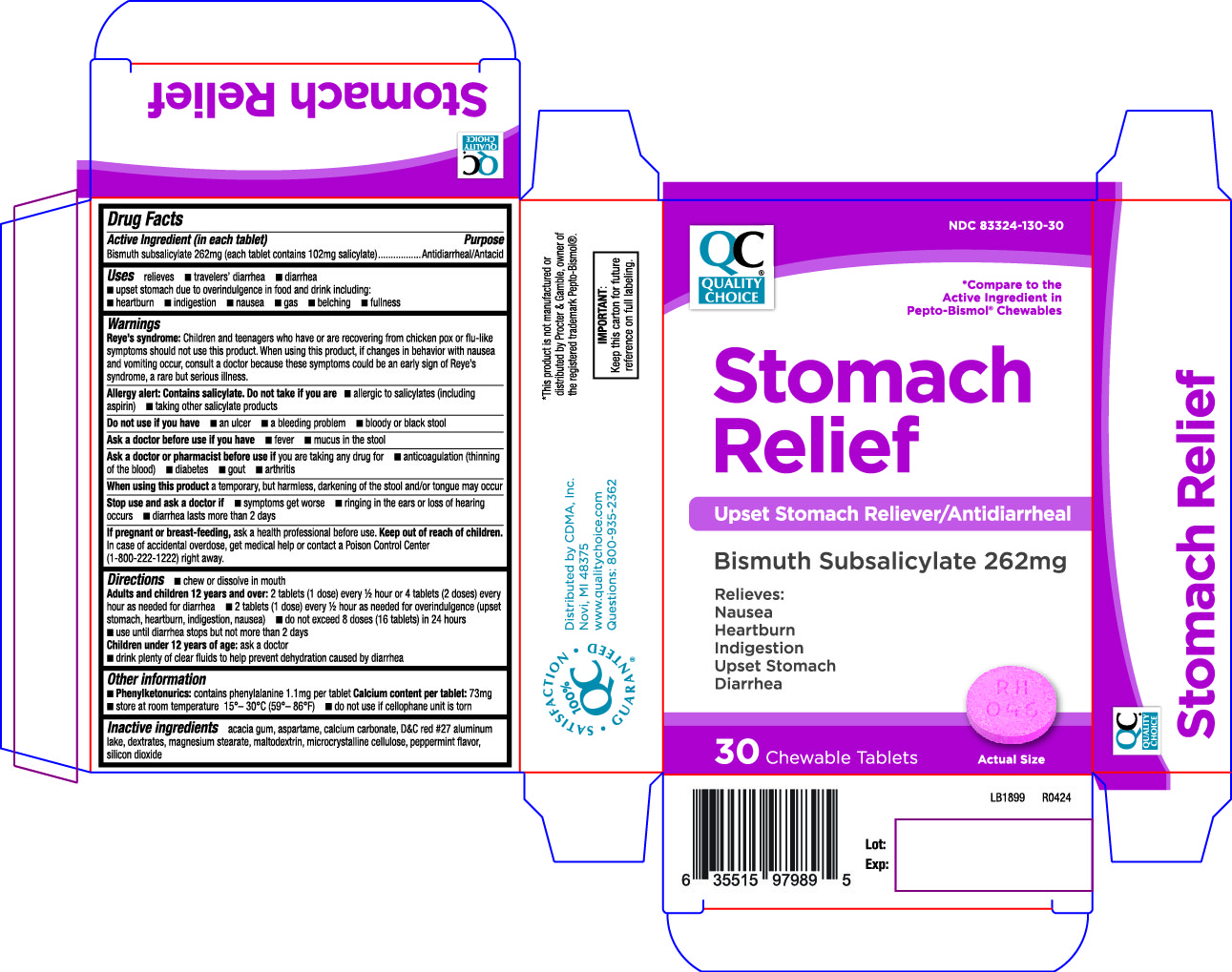 DRUG LABEL: Stomach Relief
NDC: 83324-130 | Form: TABLET
Manufacturer: Chain Drug Marketing Association, Inc.
Category: otc | Type: HUMAN OTC DRUG LABEL
Date: 20240621

ACTIVE INGREDIENTS: BISMUTH SUBSALICYLATE 262 mg/1 1
INACTIVE INGREDIENTS: ASPARTAME; ACACIA; CALCIUM CARBONATE; D&C RED NO. 27 ALUMINUM LAKE; DEXTRATES; MAGNESIUM STEARATE; MALTODEXTRIN; MICROCRYSTALLINE CELLULOSE; PEPPERMINT; SILICON DIOXIDE

046 - Stomach Relief

Active ingredient(s)

Bismuth subsalicylate 262mg (each tablet contains 102mg salicylate)

Purpose

Antidiarrheal/Antacid

Use(s)

- relieves
- travelers’ diarrhea
- diarrhea
- upset stomach due to overindulgence in food and drink including:
- heartburn
- indigestion
- nausea
- gas
- belching
- fullness

Warnings

Reye’s syndrome: Children and teenagers who have or are recovering from chicken pox or flu-like
symptoms should not use this product. When using this product, if changes in behavior with nausea
and vomiting occur, consult a doctor because these symptoms could be an early sign of Reye’s
syndrome, a rare but serious illness.

Allergy alert: Contains salicylate. Do not take if you are

- allergic to salicylates (including aspirin)
- taking other salicylate products

Do not use

- an ulcer
- a bleeding problem
- bloody or black stool

Ask a doctor before use if

- fever
- mucus in the stool

Ask a doctor or pharmacist before use if

you are taking any drug for

- anticoagulation (thinning of the blood)
- diabetes
- gout
- arthritis

When using this product

a temporary, but harmless, darkening of the stool and/or tongue may occur

Stop use and ask a doctor if

- symptoms get worse
- ringing in the ears or loss of hearing occurs
- diarrhea lasts more than 2 days

If pregnant or breastfeeding,

ask a health professional before use.

Keep out of reach of children

In case of accidental overdose, get medical help or contact a Poison Control Center
(1-800-222-1222) right away.

Directions

Chew or dissolve in mouth

Adults and children 12 years and over:

- 2 tablets (1 dose) every 1/2; hour or 4 tablets (2 doses) every
  hour as needed for diarrhea
- 2 tablets (1 dose) every 1/2; hour as needed for overindulgence (upset
  stomach, heartburn, indigestion, nausea)
- do not exceed 8 doses (16 tablets) in 24 hours
- use until diarrhea stops but not more than 2 days
- Children under 12 years of age: ask a doctor
  - drink plenty of clear fluids to help prevent dehydration caused by diarrhea

Other information

Phenylketonurics: contains phenylalanine 1.1mg per tablet

Calcium content per tablet: 73mg

- store at room temperature 15°– 30°C (59°– 86°F)
- do not use if cellophane unit is torn

Inactive ingredients

acacia gum, aspartame, calcium carbonate, D&C red #27 aluminum
lake, dextrates, magnesium stearate, maltodextrin, microcrystalline cellulose, peppermint flavor,
silicon dioxide

Principal Display Panel

Stomach Relief